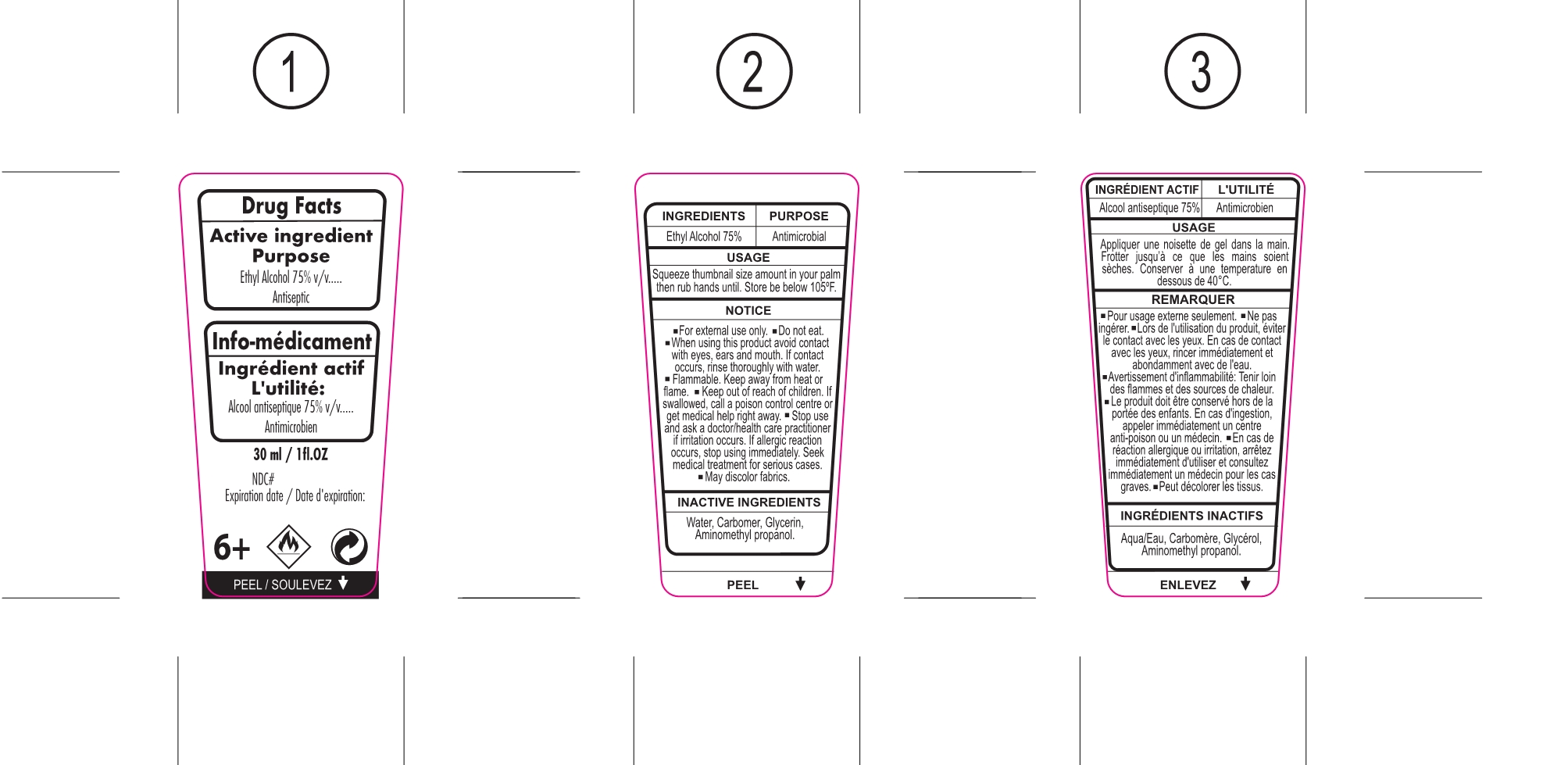 DRUG LABEL: Hand Sanitizer
NDC: 75612-030 | Form: GEL
Manufacturer: Yiwu Dieyuan Cosmetics Co., Ltd.
Category: otc | Type: HUMAN OTC DRUG LABEL
Date: 20200713

ACTIVE INGREDIENTS: ALCOHOL 22.5 mL/30 mL
INACTIVE INGREDIENTS: CARBOMER INTERPOLYMER TYPE A (ALLYL SUCROSE CROSSLINKED); GLYCERIN; AMINOMETHYLPROPANOL; WATER

75612-030

Active Ingredient(s)

Ethyl Alcohol 75% v/v. Purpose:Antimicrobial

Purpose

Antiseptic, Hand Sanitizer

Use

Squeeze thumbnail size amount in your palm then rub hands until.Store be below 105℉.

Warnings

- For external use only.
- Do not eat.
- When using this product avoid contact with eyes, ears and mouth.If contact occurs, rinse thoroughly with water.
- Flammable.Keep away from heat or flame.
- Keep out of reach of children .If swallowed, call a poison control centre or get medical help right away.
  - Stop use and ask a doctor/health care practitioner if imitation occurs.If allergic reacion occurs, stop using immediately .Seek medical treatment for serious cases.
  - May discolor fabrics.

Do not use

- in children less than 2 months of age
- on open skin wounds

When using this product keep out of eyes, ears, and mouth. In case of contact with eyes, rinse eyes thoroughly with water.
Stop use and ask a doctor if irritation or rash occurs. These may be signs of a serious condition.
Keep out of reach of children. If swallowed, get medical help or contact a Poison Control Center right away.

Stop use and ask a doctor if irritation or rash occurs. These may be signs of a serious condition.

Keep out of reach of children. If swallowed, get medical help or contact a Poison Control Center right away.

Directions

- Place enough product on hands to cover all surfaces. Rub hands together until dry.
- Supervise children under 6 years of age when using this product to avoid swallowing.

Other information

- Store between 15-30C (59-86F)
- Avoid freezing and excessive heat above 40C (105F)

Inactive ingredients

Water,Carbomer,Glycerin,Aminomethyl propanol

Package Label - Principal Display Panel

30 mL NDC: 75612-030-01